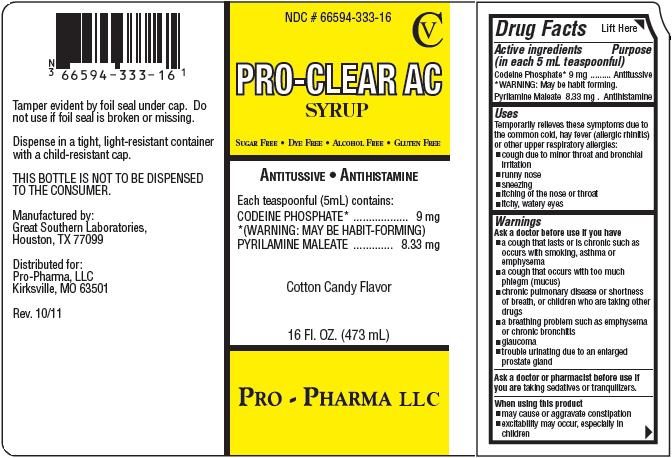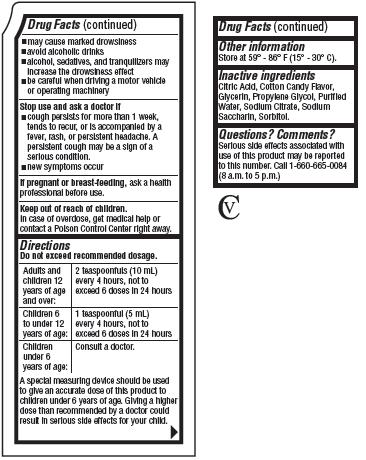 DRUG LABEL: PRO-CLEAR
NDC: 66594-333 | Form: SYRUP
Manufacturer: Pro-Pharma LLC
Category: otc | Type: HUMAN OTC DRUG LABEL
Date: 20111202
DEA Schedule: CV

ACTIVE INGREDIENTS: Codeine Phosphate 9 mg/5 mL; Pyrilamine Maleate 8.33 mg/5 mL
INACTIVE INGREDIENTS: Citric Acid; Glycerin; Propylene Glycol; Water; Sodium Citrate; Saccharin Sodium; Sorbitol

PRO-CLEAR AC SYRUP

Drug Facts

Active ingredients
(in each 5 mL teaspoonful)
Codeine Phosphate* 9 mg
*WARNING: May be habit forming.
Pyrilamine Maleate 8.33 mg

Purpose

Antitussive
Antihistamine

Uses

Temporarily relieves these symptoms due to the common cold, hay fever (allergic rhinitis) or other upper respiratory allergies:

- cough due to minor throat and bronchial irritation
- runny nose
- sneezing
- itching of the nose or throat
- itchy, water eyes

Warnings

Ask a doctor before use if you have

- a cough that lasts or is chronic such as occurs with smoking, asthma or emphysema
- a cough that occurs with too much phlegm (mucus)
- chronic pulmonary disease or shortness of breath, or children who are taking other drugs
- a breathing problem such as emphysema or chronic bronchitis
- glaucoma
- trouble urinating due to an enlarged prostate gland

Ask a doctor or pharmacist before use if you are taking sedatives or tranquilizers.

When using this product

- may cause or aggravate constipation
- excitability may occur, especially in children
- may cause marked drowsiness
- avoid alcoholic drinks
- alcohol, sedatives, and tranquilizers may increase the drowsiness effect
- be careful when driving a motor vehicle or operating machinery

Stop use and ask a doctor if

- a cough persists for more than 1 week, tends to recur, or is accompanied by a fever, rash, or persistent headache. A persistent cough may be a sign of a serious condition.
- new symptoms occur

PREGNANCY OR BREAST FEEDING

If pregnant or breast-feeding, ask a health professional before use.

Keep out of reach of children.

In case of overdose, get medical help or contact a Poison Control Center right away.

Directions

Do not exceed recommended dosage.

Adults and children 12 years of age and over: | 2 teaspoonfuls (10 mL) every 4 hours, not to exceed 6 doses in 24 hours.
Children 6 to under 12 years of age: | 1 teaspoonful (5 mL) every 4 hours, not to exceed 6 doses in 24 hours
Children under 6 years of age: | Consult a doctor.

A special measuring device should be used to give an accurate dose of this product to children under 6 years of age. Giving a higher dose than recommended by a doctor could result in serious side effects for your child.

Other information

Store at 59°-86°F (15°-30°C).

Inactive ingredients

Citric Acid, Cotton Candy Flavor, Glycerin, Propylene Glycol, Purified Water, Sodium Citrate, Sodium Saccharin, Sorbitol.

Questions? Comments?

Serious side effects associated with use of this product may be reported to this number. Call 1-660-665-0084 (8 a.m. to 5 p.m.)
CV

Product Packaging:

The packaging below represents the labeling currently used.
Principal display panel and side panel for 473 mL label:
NDC # 66594-333-16
CV
PRO-CLEAR AC
SYRUP
SUGAR FREE · DYE FREE · ALCOHOL FREE · GLUTEN FREE
ANTITISSIVE · ANTIHISTAMINE
Each teaspoonful (5 mL) contains:
CODEINE PHOSPHATE*.............................9 mg
*(WARNING: MAY BE HABIT-FORMING)
PYRILAMINE MALEATE..........................8.33 mg
Cotton Candy Flavor
16 FL. OZ. (473 mL)
PRO-PHARMA LLC
Tamper evident by foil seal under cap. Do not use if foil seal is broken or missing.
Dispense in a tight, light-resistant container with a child-resistant cap.
THIS BOTTLE IS NOT TO BE DISPENSED TO THE CONSUMER.
Manufactured by:
Great Southern Laboratories,
Houston, TX 77099
Distributed for:
Pro-Pharma, LLC
Kirksville, MO 63501
Rev. 10/11